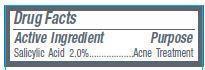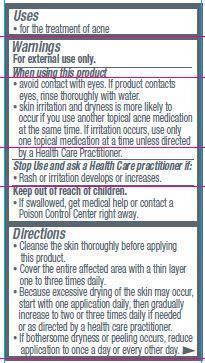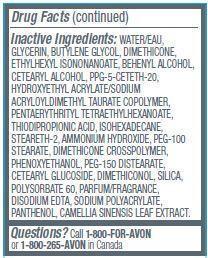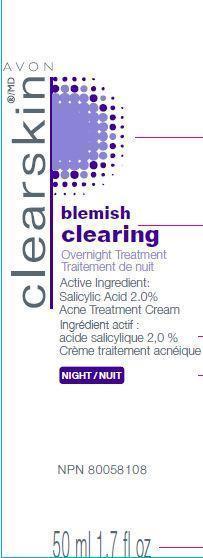 DRUG LABEL: Clearskin Blemish Clearing
NDC: 10096-0327 | Form: CREAM
Manufacturer: New Avon LLC
Category: otc | Type: HUMAN OTC DRUG LABEL
Date: 20190101

ACTIVE INGREDIENTS: SALICYLIC ACID 20 mg/1 mL
INACTIVE INGREDIENTS: WATER

Clearskin Blemish Clearing Overnight Treatment

Active ingredient

Salicylic Acid 2.0%.......................

Purpose
........................Acne Treatment

Uses

- for the treatment of acne

Warnings
For external use only

When using this product

- avoid contact with eyes. If product contacts eyes, rinse thoroughly with water.
- skin irritation and dryness is more likely to occur if you use another topical acne medication at the same time. If irritation occurs, use only one topical medication at a time unless directed by a Health Care Practitioner.

Stop Use and ask a Health Care practitioner if:

- Rash or irritation develops or increases.

Keep out of reach of children.

- If swallowed, get medical help or contact a Poison Control Center right away.

Directions

- Cleanse the skin thoroughly before applying this product.
- Cover the entire affected area with a thin layer one to three times daily.
- Because excessive drying of the skin may occur, start with one application daily, then gradually increase to two or three times daily if needed or as directed by a health care practitioner.
- If bothersome dryness or peeling occurs, reduce application to once a day or every other day.

INACTIVE INGREDIENT

Inactive Ingredients: WATER/EAU, GLYCERIN, BUTYLENE GLYCOL, DIMETHICONE, ETHYLHEXYL ISONONANOATE, BEHENYL ALCOHOL, CETEARYL ALCOHOL, PPG-5-CETETH-20, HYDROXYETHYL ACRYLATE/SODIUM ACRYLOYLDIMETHYL TAURATE COPOLYMER, PENTAERYTHRITYL TETRAETHYLHEXANOATE, THIODIPROPIONIC ACID, ISOHEXADECANE, STEARETH-2, AMMONIUM HYDROXIDE, PEG-100 STEARATE, DIMETHICONE CROSSPOLYMER, PHENOXYETHANOL, PEG-150 DISTEARATE, CETEARYL GLUCOSIDE, DIMETHICONOL, SILICA, POLYSORBATE 60, PARFUM/FRAGRANCE, DISODIUM EDTA, SODIUM POLYACRYLATE, PANTHENOL, CAMELLIA SINENSIS LEAF EXTRACT.

QUESTIONS

Questions? Call 1-800-FOR-AVON or 1-800-265-AVON in Canada.